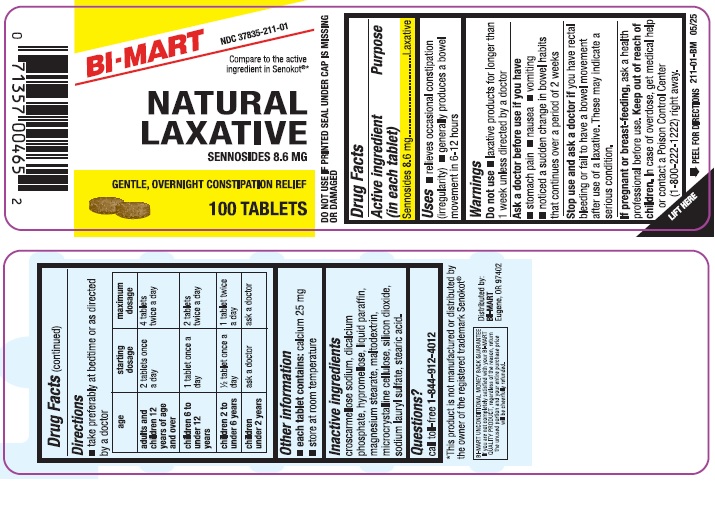 DRUG LABEL: Natural Laxative
NDC: 37835-211 | Form: TABLET, FILM COATED
Manufacturer: Bi-Mart
Category: otc | Type: HUMAN OTC DRUG LABEL
Date: 20251010

ACTIVE INGREDIENTS: SENNOSIDES 8.6 mg/1 1
INACTIVE INGREDIENTS: MALTODEXTRIN; CELLULOSE, MICROCRYSTALLINE; CROSCARMELLOSE SODIUM; STEARIC ACID; SILICON DIOXIDE; MAGNESIUM STEARATE; HYPROMELLOSES; SODIUM LAURYL SULFATE; DIBASIC CALCIUM PHOSPHATE DIHYDRATE; MINERAL OIL

Drug Facts

Active ingredient (in each tablet)

Sennosides 8.6 mg

Purpose

Laxative

Uses

- relieves occasional constipation (irregularity)
- generally produces a bowel movement in 6-12 hours

Warnings

Do not use

- laxative products for longer than 1 week unless directed by a doctor

Ask a doctor before use if you have

- stomach pain
- nausea
- vomiting
- noticed a sudden change in bowel habits that continues over a period of 2 weeks

Stop use and ask a doctor if

you have rectal bleeding or fail to have a bowel movement after use of a laxative. These may indicate a serious condition.

If pregnant or breast-feeding,

ask a health professional before use.

Keep out of reach of children.

In case of overdose, get medial help or contact a Poison Control Center (1-80-222-1222) right away.

Directions

- take preferably at bedtime or as directed by a doctor

age | starting dosage | maximum dosage
adults and children 12 years of age or older | 2 tablets once a day | 4 tablets twice a day
children 6 to under 12 years | 1 tablet once a day | 2 tablets twice a day
children 2 to under 6 years | 1/2 tablet once a day | 1 tablet twice a day
children under 2 years | ask a doctor | ask a doctor

Other information

- each tablet contains:calcium 25 mg
- store at room temperature

Inactive ingredients

croscarmellose sodium, dicalcium phosphate, hypromellose, liquid paraffin, magnesium stearate, maltodextrin, microcrystalline cellulose, silicon dioxide, sodium lauryl sulfate, stearic acid.

Questions?

call toll free 1-844-912-4012